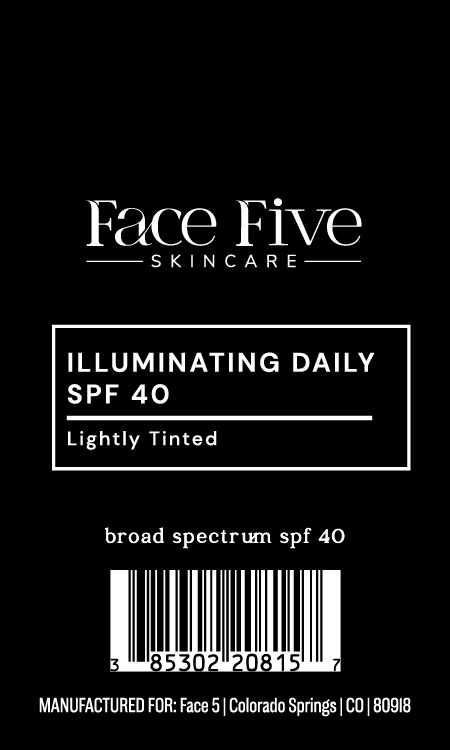 DRUG LABEL: Illuminating Daily SPF 40 Lightly Tinted
NDC: 85302-208 | Form: CREAM
Manufacturer: Face 5, LLC
Category: otc | Type: HUMAN OTC DRUG LABEL
Date: 20251208

ACTIVE INGREDIENTS: ZINC OXIDE 160 mg/1 g
INACTIVE INGREDIENTS: CI 77491; ALPHA-TOCOPHEROL ACETATE; VINYL DIMETHICONE/METHICONE SILSESQUIOXANE CROSSPOLYMER; DIMETHICONOL (2000 CST); HYDROGEN DIMETHICONE (20 CST); POLYHYDROXYSTEARIC ACID (2300 MW); TETRAHEXYLDECYL ASCORBATE; CYCLOHEXASILOXANE; DIMETHICONE/VINYL DIMETHICONE CROSSPOLYMER (SOFT PARTICLE); PEG-10 DIMETHICONE (600 CST); CERAMIDE 3; DIMETHICONE; CYCLOPENTASILOXANE; DIMETHICONE CROSSPOLYMER; CAPRYLIC/CAPRIC TRIGLYCERIDE; CI 77499; CI 77492

Active Ingredients:

Zinc Oxide 16%

Purpose:

Sunscreen

Warning:

- For external use only
- Keepout of reach of children

Warnings:

- For external use only
- Keepout of reach of children

Directions:

Apply liberally 15 minutes befofre sun exposure.

INACTIVE INGREDIENT

Capric/Caprylic Triglyceride, Ceramide 3, Cyclohexasiloxane, Cyclopentasiloxane, Dimethicone, Dimethicone Crosspolymer, Dimethicone/Vinyl Dimethicone Crosspolymer, Dimethiconol, Iron Oxide, Hydrogen Dimethicone, PEG-10 Dimethicone, Polyhydroxystearic Acid, Tetrahexyldecyl Ascorbate, Tocopheryl Acetate, Vinyl Dimethicone/Methicone Silsesquioxane Crosspolymer

OTHER SAFETY INFORMATION

SAMPLE NOT FOR RESALE

Warning:

Keep out of reach of children